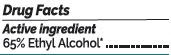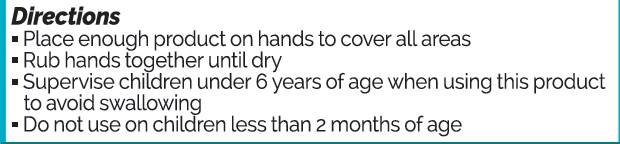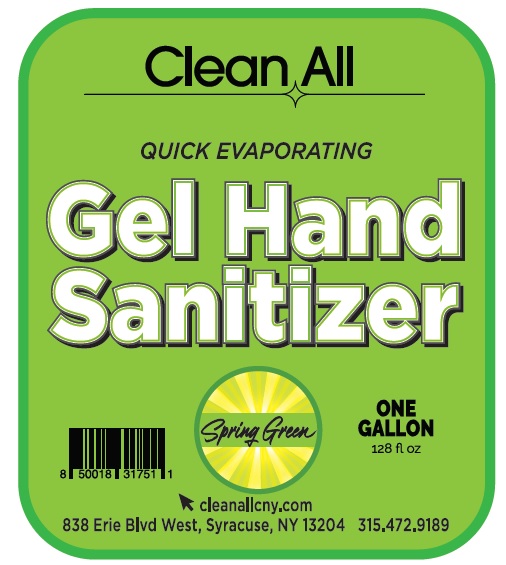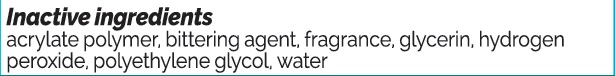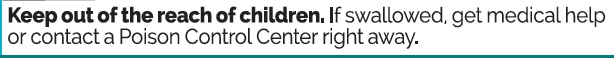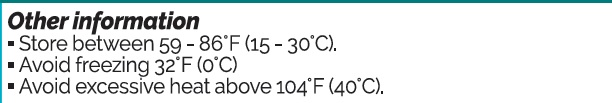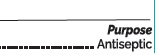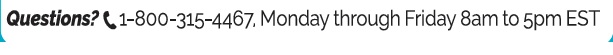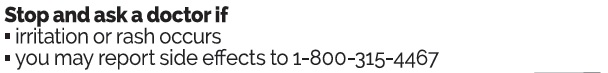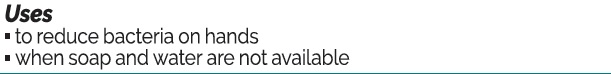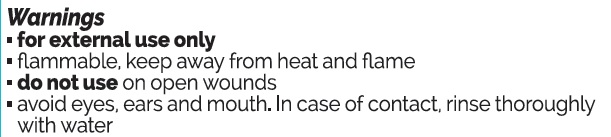 DRUG LABEL: Hand Sanitizer
NDC: 75660-054 | Form: GEL
Manufacturer: Solents and Petroleum Service INC
Category: otc | Type: HUMAN OTC DRUG LABEL
Date: 20200928

ACTIVE INGREDIENTS: ALCOHOL 2460.52 mL/3785.41 mL
INACTIVE INGREDIENTS: ACRYLATES/VINYL ISODECANOATE CROSSPOLYMER (10000 MPA.S NEUTRALIZED AT 0.5%) 18.93 mL/3785.41 mL; DENATONIUM BENZOATE 0.38 mL/3785.41 mL; POLYETHYLENE GLYCOL, UNSPECIFIED 75.71 mL/3785.41 mL; GLYCERIN 51.1 mL/3785.41 mL; HYDROGEN PEROXIDE 6.81 mL/3785.41 mL; WATER 1172.34 mL/3785.41 mL

Charcoal Filtered Gel Hand Sanitizer

Purpose

Purpose... Antiseptic

Use

Uses

to reduce bacteria on hands

when soap and water are not available

Warnings

Stop and ask doctor if

irriation or rash occurs

you may report side effects to 1-800-315-4467

Keep out of reach of children. If swallowed, get medical help or contact a Poison Control Center right away.

Other information

Store between 15-30C (59-86F)
Avoid freezing 32 F (0 C)
Avoid excessive heat above 140 F (40 C)

Inactive ingredients

acrylate polymer, bittering agent, fragrance, glycerin, hydrogen peroxide, polyethelyne glycol, water

Directions

Place enough product on hands to cover all areas
Rub hands together until dry.
Supervise children under 6 years of age when using this product to avoid swallowing.
Do not use on children less than 2 months

Questions?

Questions? 1-800-315-4467 Monday through Friday 8am to 5pm ES